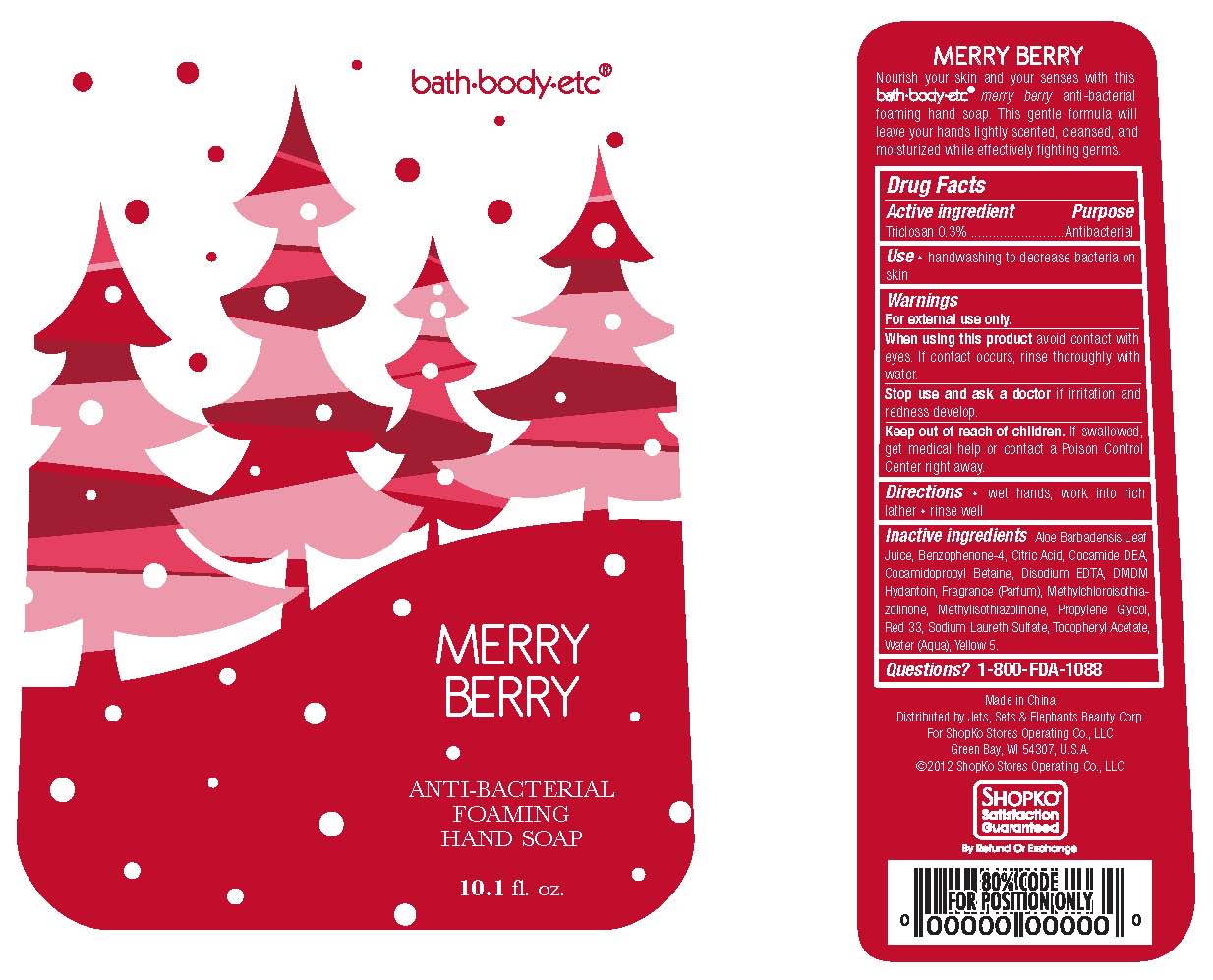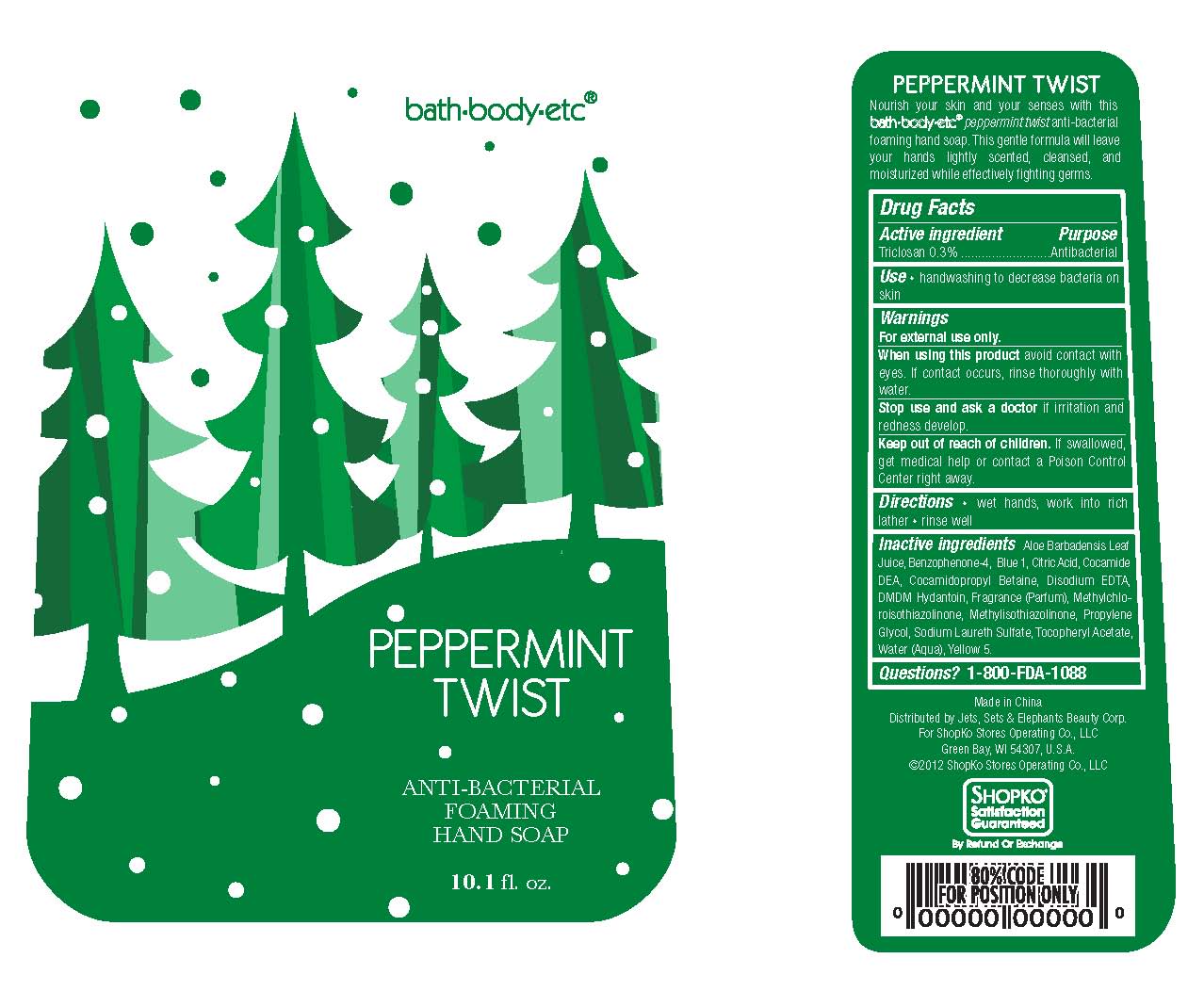 DRUG LABEL: Shopko Antibacterial Foaming Hand Cleanser
NDC: 50988-303 | Form: SOLUTION
Manufacturer: Jets, Sets, & Elephants Beauty Corp.
Category: otc | Type: HUMAN OTC DRUG LABEL
Date: 20120709

ACTIVE INGREDIENTS: TRICLOSAN 0.3 mL/100 mL
INACTIVE INGREDIENTS: WATER; SODIUM LAURETH SULFATE; COCAMIDOPROPYL BETAINE; COCO DIETHANOLAMIDE; PROPYLENE GLYCOL; DMDM HYDANTOIN; ALOE VERA LEAF; METHYLISOTHIAZOLINONE; METHYLCHLOROISOTHIAZOLINONE; ACETYL TRIETHYLHEXYL CITRATE; EDETATE DISODIUM; SULISOBENZONE; .ALPHA.-TOCOPHEROL ACETATE; VITAMIN A PALMITATE; D&C RED NO. 33; FD&C YELLOW NO. 5

SHOPKO® Anti-Bacterial Foaming Hand Soap - Merry Berry and Peppermint Twist

Active ingredient

Triclosan 0.3%

Purpose

Antibacterial

Use

- handwashing to decrease bacteria on skin

Warnings

For external use only.

When using this product

avoid contact with eyes. If contact occurs, rinse thoroughly with water.

Stop use and ask a doctor

if irritation and redness develop.

Keep out of reach of children.

If swallowed, get medical help or contact a Poison Control Center right away.

Directions

- wet hands, work into rich lather
- rinse well

Inactive ingredients (Merry Berry)

Aloe Barbadensis Leaf Juice, Benzophenone-4, Citric Acid, Cocamide DEA, Cocamidopropyl Betaine, Disodium EDTA, DMDM Hydantoin, Fragrance (Parfum), Methylchloroisothiazolinone, Methylisothiazolinone, Propylene Glycol, Red 33, Sodium Laureth Sulfate, Tocopheryl Acetate, Water (Aqua), Yellow 5.

Inactive ingredients (Peppermint Twist)

Aloe Barbadensis Leaf Juice, Benzophenone-4, Blue-1, Citric Acid, Cocamide DEA, Cocamidopropyl Betaine, Disodium EDTA, DMDM Hydantoin, Fragrance (Parfum), Methylchloroisothiazolinone, Methylisothiazolinone, Propylene Glycol, Sodium Laureth Sulfate, Tocopheryl Acetate, Water (Aqua), Yellow 5

QUESTIONS?

1-800-FDA-1088

PACKAGE/LABEL PRINCIPAL DISPLAY PANEL

bath·body·etc®

Merry Berry

ANTI-BACTERIAL FOAMING

HAND SOAP

10.1 fl.oz

Made in China

Distributed by Jets, Sets & Elephants Beauty Corp.

For ShopKo Stores Operating Co., LLC

Green Bay, WI 54307, U.S.A

©2012 ShopKo Stores Operating Co., LLC

SATISFACTION GUARANTEED BY REFUND OR EXCHANGE

Bottle Label

PACKAGE/LABEL PRINCIPAL DISPLAY PANEL

bath·body·etc®

Peppermint Twist

ANTI-BACTERIAL FOAMING

HAND SOAP

10.1 fl.oz

Made in China

Distributed by Jets, Sets & Elephants Beauty Corp.

For ShopKo Stores Operating Co., LLC

Green Bay, WI 54307, U.S.A

©2012 ShopKo Stores Operating Co., LLC

SATISFACTION GUARANTEED BY REFUND OR EXCHANGE

Bottle Label